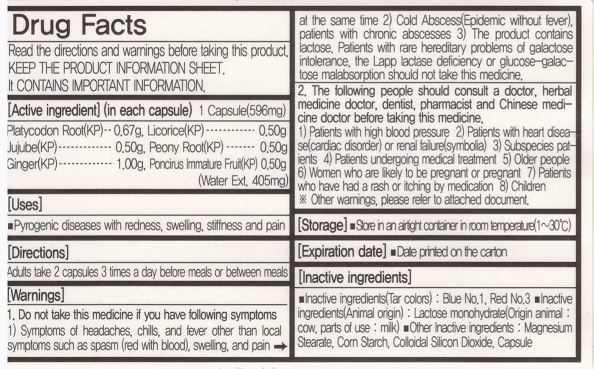 DRUG LABEL: BAENOSIN
NDC: 72988-0011 | Form: CAPSULE
Manufacturer: Lydia Co., Ltd.
Category: otc | Type: HUMAN OTC DRUG LABEL
Date: 20231216

ACTIVE INGREDIENTS: LICORICE 0.5 g/1 1; PAEONIA LACTIFLORA ROOT 0.5 g/1 1; PLATYCODON GRANDIFLORUM ROOT 0.67 g/1 1; JUJUBE FRUIT 0.5 g/1 1; GINGER 0.5 g/1 1; PONCIRUS TRIFOLIATA FRUIT 0.5 g/1 1
INACTIVE INGREDIENTS: LACTOSE MONOHYDRATE; MAGNESIUM STEARATE

Drug Facts

ACTIVE INGREDIENT

platycodon root, licorice, jujube, peony root, ginger, poncirus immature fruit

INACTIVE INGREDIENT

lactose monohydrate, acacia, corn starch, carboxymethylcellulose calcium, l-menthol

PURPOSE

pyrogenic diseases with redness, swelling, stiffness and pain

keep out of reach of the children

INDICATIONS AND USAGE

adults take 2 capsules 3 times a day before meals or between meals

WARNINGS

do not take this medicine if you have following symptoms

symptoms of headaches, chills, and fever other than local symptoms such as spasm (red with blood), swelling, and pain at the same time

DOSAGE AND ADMINISTRATION

for oral use only